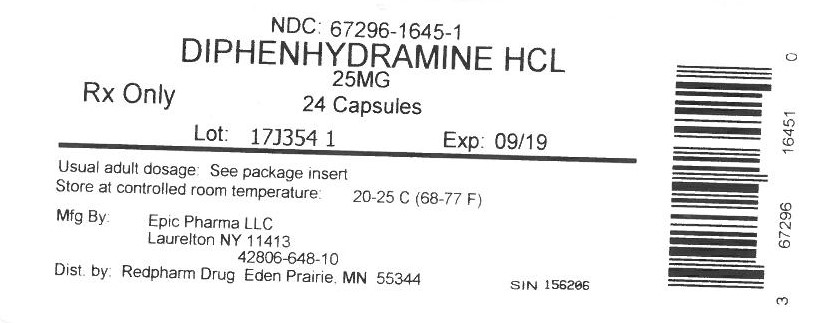 DRUG LABEL: Diphenhydramine Hydrochloride
NDC: 67296-1645 | Form: CAPSULE
Manufacturer: RedPharm Drug, Inc.
Category: otc | Type: HUMAN OTC DRUG LABEL
Date: 20210114

ACTIVE INGREDIENTS: DIPHENHYDRAMINE HYDROCHLORIDE 25 mg/1 1
INACTIVE INGREDIENTS: BENZYL ALCOHOL; BUTYLPARABEN; D&C RED NO. 28; FD&C BLUE NO. 1; FD&C RED NO. 40; GELATIN; LACTOSE; MAGNESIUM STEARATE; METHYLPARABEN; POLYSORBATE 80; PROPYLPARABEN; SODIUM LAURYL SULFATE

Diphenhydramine 25mg

ACTIVE INGREDIENT (IN EACH CAPSULE)

Diphenhydramine HCl 25 mg

PURPOSE

Antihistamine

USES

temporarily relieves these symptoms of hay fever or other upper respiratory allergies:

- runny nose
- sneezing
- itchy nose or throat
- itchy, watery eyes

WARNINGS

Do not use with any other product containing diphenhydramine, even one used on skin

Ask a doctor before use if you have

- glaucoma
- trouble urinating due to an enlarged prostate gland
- a breathing problem such as emphysema or chronic bronchitis

Ask a doctor or pharmacist before use if you are taking sedatives or tranqulizers

When using this product

- you may get very drowsy
- avoid alcoholic drinks
- alcohol, sedatives and tranquilizers may increase drowsiness
- be careful when driving a motor vehicle or operating machinery
- excitability may occur, especially in children

If pregnant or breast-feeding, ask a health professional before use.

KEEP OUT OF THE REACH OF CHILDREN.

In case of overdose, get medical help or contact a Poison Control Venter right away.

DIRECTIONS

- adults & children 12 years and over: take 1-2 capsules every 4-6 hours; not more than 6 does in 24 hours
- children under 12 years: ask a doctor

OTHER INFORMATION

- store at 15°-30°C (59°-86°F)
- protect from moisture
- This is a bulk package. Dispense contents in a tight, light-resistant container with a child-resistant closure as defined in the USP

INACTIVE INGREDIENTS

benzyl alcohol, butylparaben, D&C red #28, edible black ink, FD&C blue #1, FD&C red #40, gelatin, lactose, magnesium stearate, methylparaben, polysorbate 80, propylparaben, sodium lauryl sulfate

QUESTIONS OR COMMENTS?

call 888-374-279 1, 8:30 am - 4:30 pm ET, Monday - Friday

TAMPER EVIDENT: DO NOT USE IF IMPRINTED SAFTEY SEAL UNDER CAP OR BAND AROUND ANY CAPSULE IS MISSING OR DAMAGED

Distributed by:

Epic Pharma, LLC

Laurelton, NY

11413